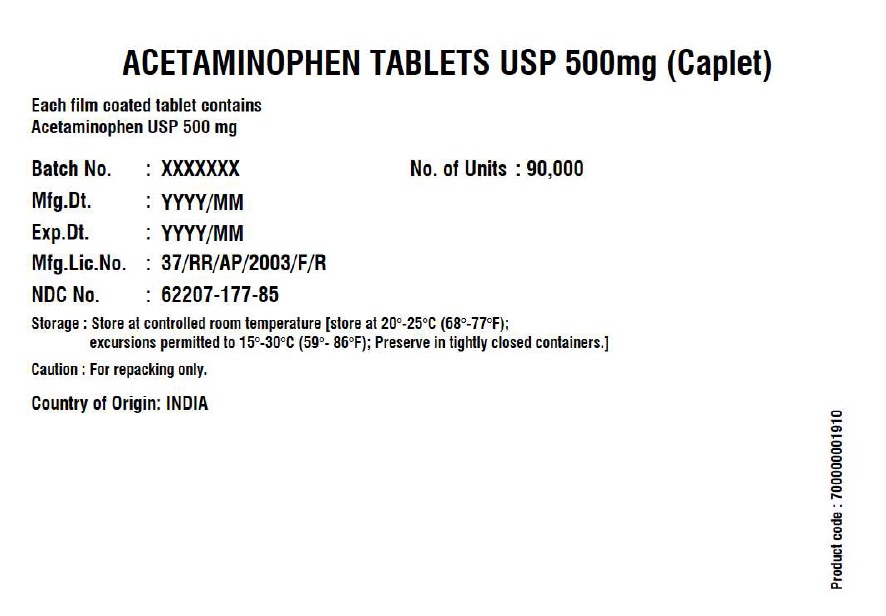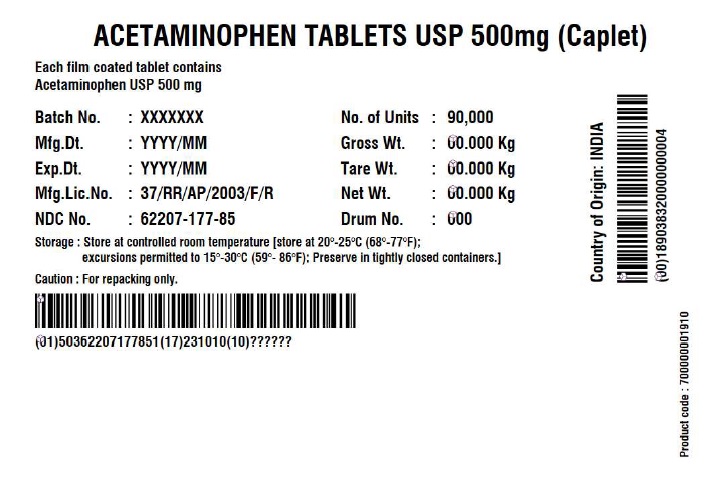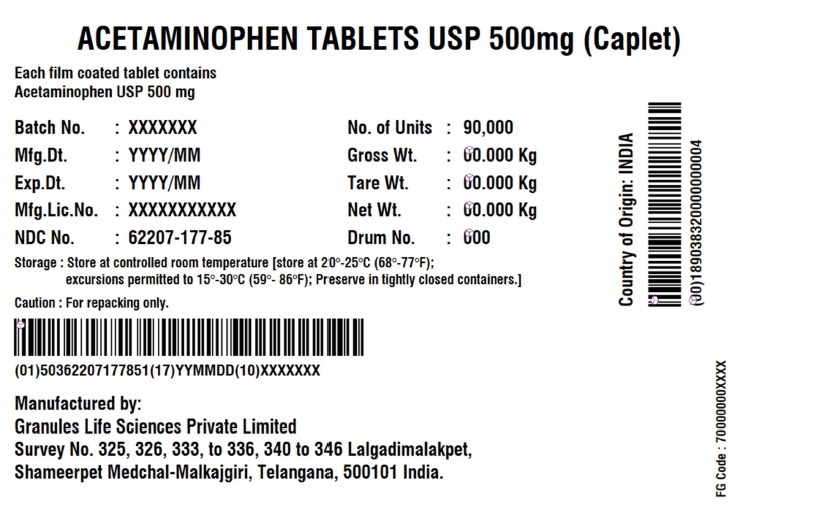 DRUG LABEL: Acetaminophen
NDC: 62207-177 | Form: TABLET
Manufacturer: Granules India Limited
Category: otc | Type: HUMAN OTC DRUG LABEL
Date: 20251016

ACTIVE INGREDIENTS: ACETAMINOPHEN 500 mg/1 1
INACTIVE INGREDIENTS: POLYETHYLENE GLYCOL, UNSPECIFIED; STEARIC ACID; SODIUM STARCH GLYCOLATE TYPE A POTATO; STARCH, CORN; POVIDONE K30; HYPROMELLOSE, UNSPECIFIED

Acetaminophen Tablets USP 500 mg (Caplet)